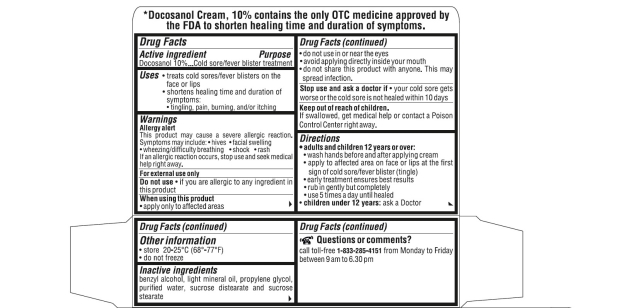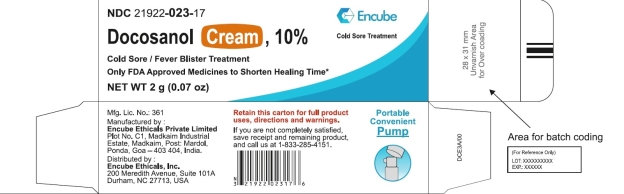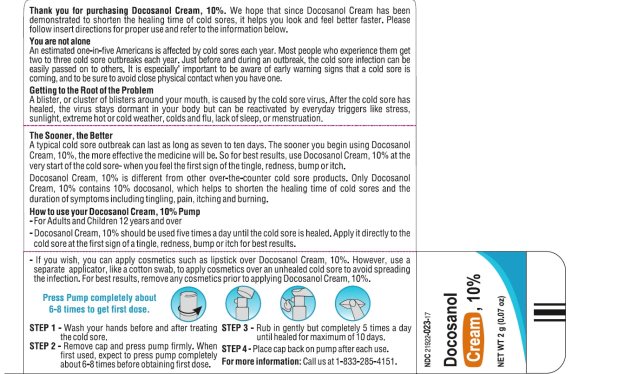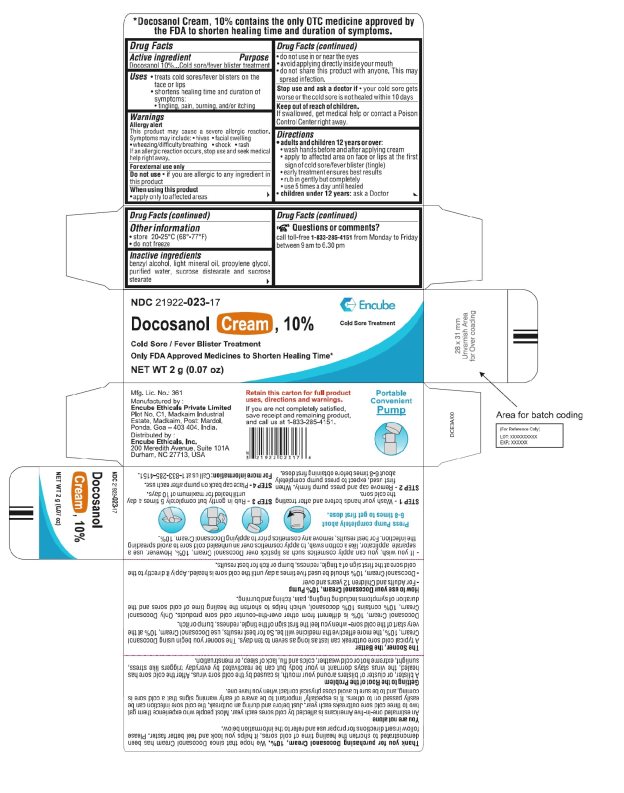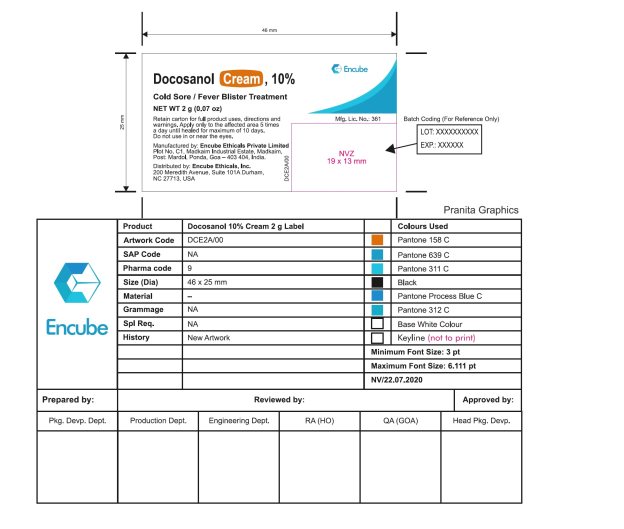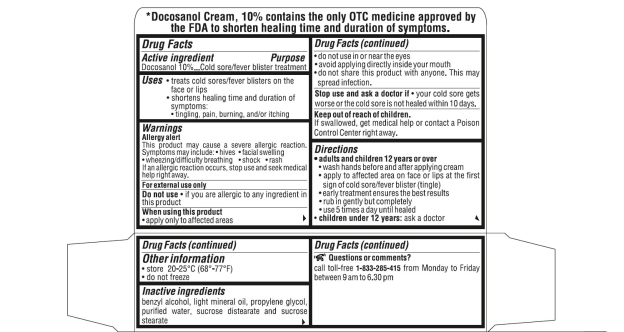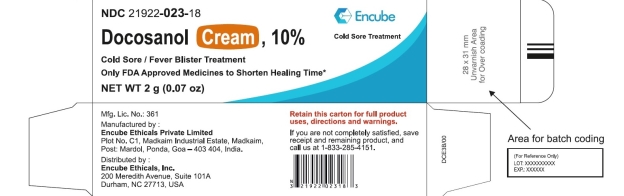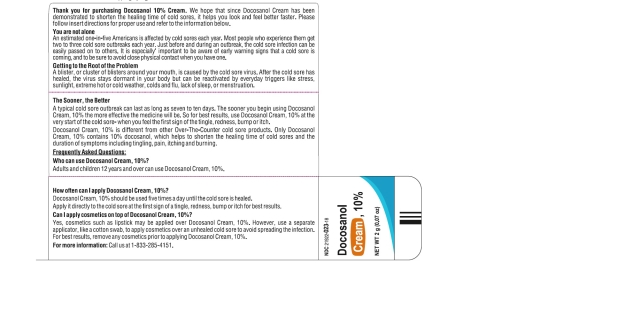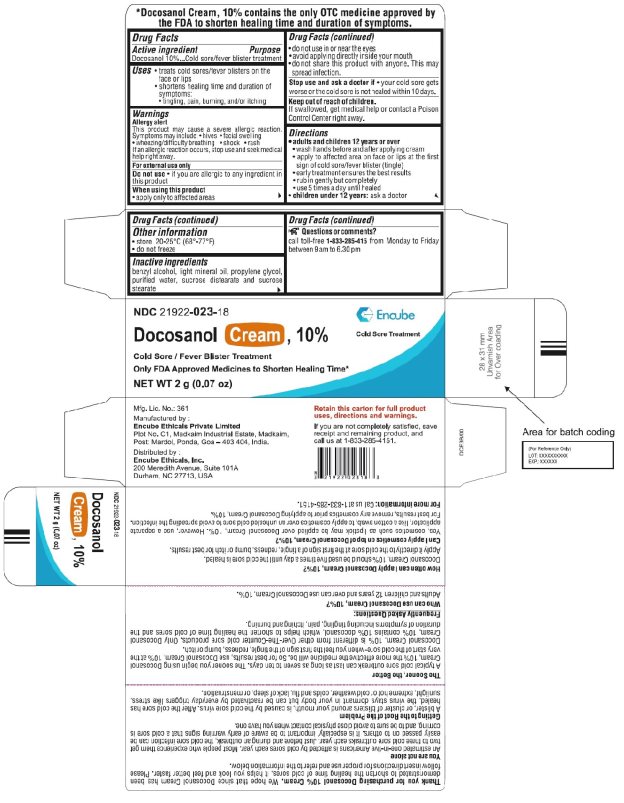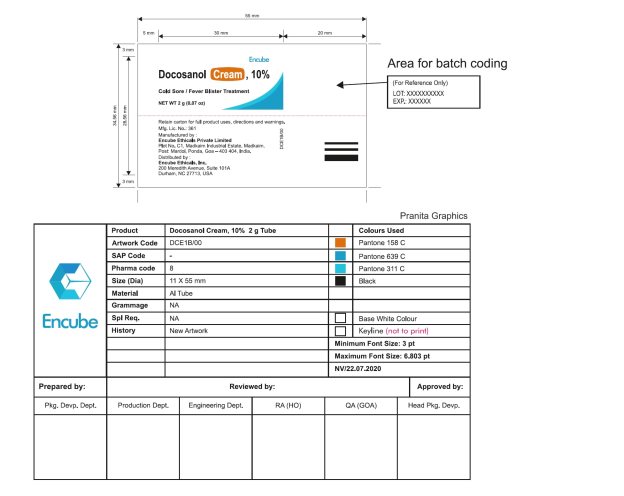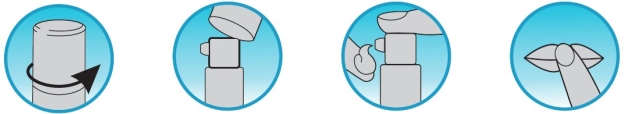 DRUG LABEL: Docosanol
NDC: 21922-023 | Form: CREAM
Manufacturer: Encube Ethicals, Inc.
Category: otc | Type: HUMAN OTC DRUG LABEL
Date: 20250908

ACTIVE INGREDIENTS: DOCOSANOL 100 mg/1 g
INACTIVE INGREDIENTS: BENZYL ALCOHOL; LIGHT MINERAL OIL; PROPYLENE GLYCOL; WATER; SUCROSE DISTEARATE; SUCROSE STEARATE

DOCOSANOL 10% CREAM

ACTIVE INGREDIENT(S)

Docosanol 10%

PURPOSE

Cold sore/fever blister treatment

USE(S)

- treats cold sores/fever blisters on the face or lips
- shortens healing time and duration of symptoms:
- tingling, pain, burning, and/or itching

WARNINGS

Allergy alert

This product may cause a severe allergic reaction.

Syptoms may include:

- hives
- facial swelling
- wheezing/difficulty breathing
- shock
- rash

If an allergic reaction occurs, stop use and seek medical help right away.

For external use only

DO NOT USE

- if you are allergic to any ingredient in this product

When using this product

- apply only to affected areas
- do not use in or near the eyes
- avoid applying directly inside your mouth
- do not share this product with anyone. This may spread infection.

STOP USE AND ASK DOCTOR IF

- your cold sore gets worse or the cold sore is not healed within 10 days

KEEP OUT OF REACH OF CHILDREN

If swallowed, get medical help or contact a Poison Control Center right away.

DIRECTIONS

adults and children 12 years or over:

- wash hands before and after applying cream
- apply to affected area on face or lips at the first sign of cold sore/fever blister (tingle).
- early treatment ensures the best results
- rub in gently but completely
- use 5 times a day until healed

children under 12 years : ask a doctor

STORAGE

- store at 20°-25°C (68°-77°F)

do not freeze

INACTIVE INGREDIENTS

benzyl alcohol, light mineral oil, propylene glycol, purified water, sucrose distearate and sucrose stearate

QUESTIONS OR COMMENTS?

call toll-free 1-833-285-4151 from Monday to Friday between 9 am to 6.30 pm

Manufactured by:

Encube Ethicals Private Limited

Plot No. C1,Madkaim Industrial Estate, Madkaim,

Post: Mardol, Ponda, Goa – 403 404, India

Distributed by:

Encube Ethicals, Inc.

200 Meredith Avenue, Suite 101A

Durham, NC 27713, USA

Thank you for purchasing Docosanol Cream, 10%. We hope that since Docosanol Cream shortens the healing time of cold sores, it helps you look and feel better faster. Please follow insert directions for proper use and refer to the information below.

You are not alone

An estimated one-in-five Americans is affected by cold sores each year. Most people who experience them get two to three cold sore outbreaks each year. Just before and during an outbreak, the cold sore infection can be easily passed on to others. It is especially important to be aware of early warning signs that a cold sore is coming, and to be sure to avoid close physical contact when you have one.

Getting to the Root of the Problem

A blister, or cluster of blisters around your mouth, is caused by the cold sore virus. After the cold sore has healed, the virus stays dormant in your body but can be reactivated by everyday triggers like stress, sunlight, extreme hot or cold weather, colds and flu, lack of sleep, or menstruation.

The Sooner, the Better

A typical cold sore outbreak can last as long as seven to ten days. The sooner you begin using Docosanol Cream, 10%, the more effective the medicine will be. So for best results, use Docosanol Cream, 10% at the very start of the cold sore - when you feel the first sign of the tingle, redness, bump or itch.
Docosanol Cream, 10% is different from other over-the-counter cold sore products. Only Docosanol Cream, 10% contains 10% docosanol, which helps to shorten the healing time of cold sores and the duration of symptoms including tingling, pain, itching and burning.

FREQUENTLY ASKED QUESTIONS:

For Pump Bottle

How to use your Docosanol Cream, 10% Pump
- Adults and children 12 years and over can use Docosanol Cream, 10%.
- Docosanol Cream, 10% should be used five times a day until the cold sore is healed. Apply it directly to the cold sore at the first sign of a tingle, redness, bump or itch for best results.
- If you wish, you can apply cosmetics such as lipstick over Docosanol Cream, 10%. However, use a separate applicator, like a cotton swab, to apply cosmetics over an unhealed cold sore to avoid spreading the infection. For best results, remove any cosmetics prior to applying Docosanol Cream, 10%.

Press Pump completely about 6-8 times to get first dose.

STEP 1 – Wash your hands before and after treating the cold sore.

STEP 2 – Remove cap and press pump firmly. When first used, expect to press pump completely about 6-8 times before obtaining first dose.

STEP 3 – Rub in gently but completely 5 times a day until healed for maximum of 10 days.

STEP 4 – Place cap back on pump after each use.

For Tube

Who can use Docosanol Cream, 10%?

Adults and children 12 years and over can use Docosanol Cream, 10%.

How often can I apply Docosanol Cream, 10%?

Docosanol Cream, 10% should be used five times a day until the cold sore is healed. Apply it directly to the cold sore at the first sign of a tingle, redness, bump or itch for best results.

Can I apply cosmetics on top of Docosanol Cream, 10%?

Yes, cosmetics such as lipstick may be applied over Docosanol Cream, 10%. However, use a separate applicator, like a cotton swab, to apply cosmetics over an unhealed cold sore to avoid spreading the infection. For best results, remove any cosmetics prior to applying Docosanol Cream, 10%.

PRINCIPAL DISPLAY PANEL

For Pump Bottle- Carton Label
NDC 21922-023-17
DOCOSANOL 10% CREAM
Cold Sore/Fever Blister Treatment
Only FDA Approved to Shorten Healing Time*
Cold Sore Treatment
NET WT
2g (0.07oz)
For Pump Bottle- Bottle Label
NDC 21922-023-17
DOCOSANOL 10% CREAM
Cold Sore/Fever Blister Treatment
Only FDA Approved to Shorten Healing Time*
Cold Sore Treatment
NET WT
2g (0.07oz)
For Tube - Carton
NDC 21922-023-18
DOCOSANOL 10% CREAM
Cold Sore/Fever Blister Treatment
Only FDA Approved to Shorten Healing Time*
Cold Sore Treatment
NET WT
2g (0.07 oz)

For Tube
NDC 21922-023-18
DOCOSANOL 10% CREAM
Cold Sore/Fever Blister Treatment
Only FDA Approved to Shorten Healing Time*
Cold Sore Treatment
NET WT
2g (0.07 oz)